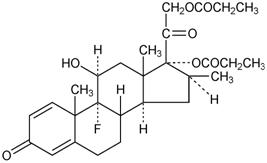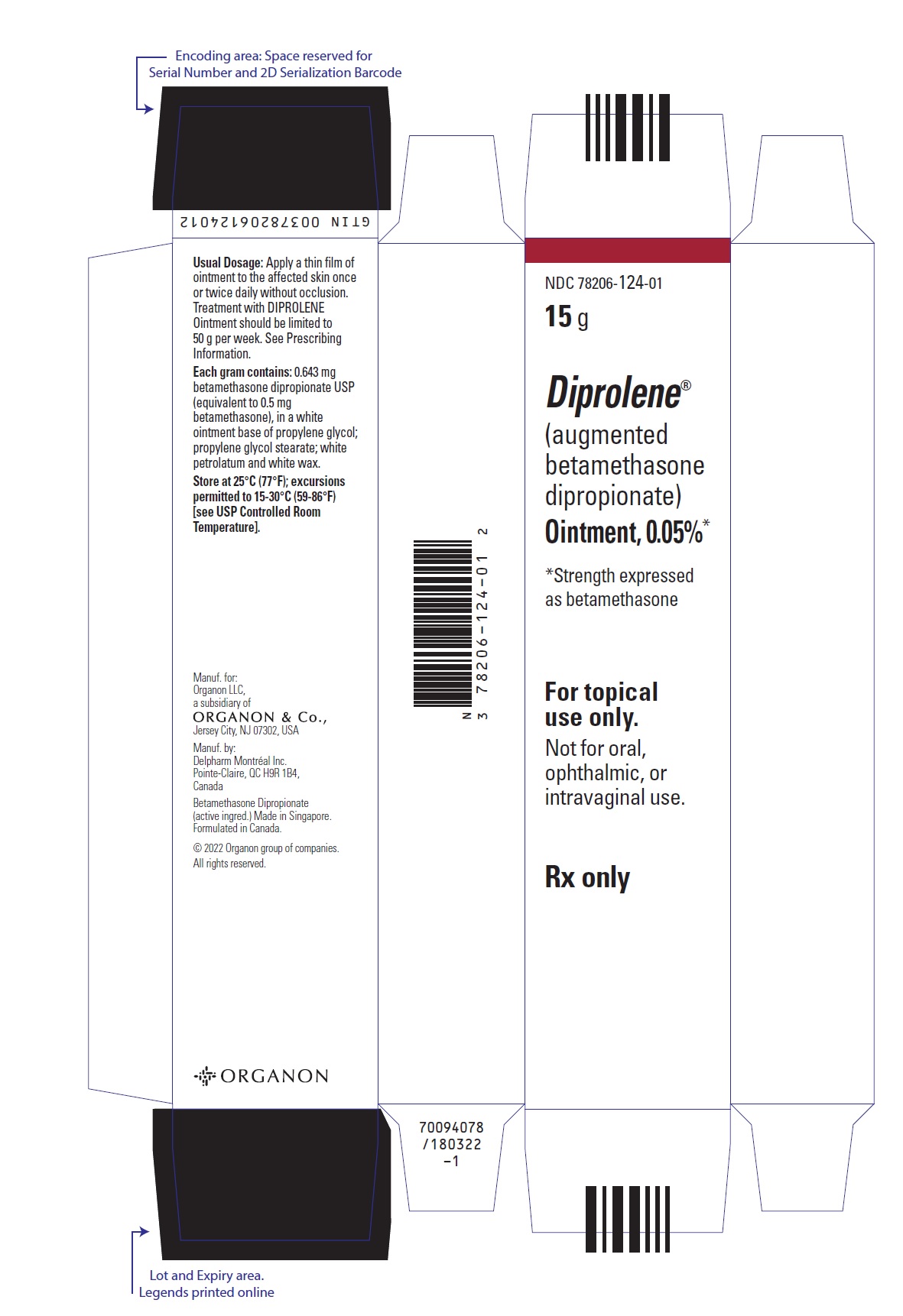 DRUG LABEL: DIPROLENE
NDC: 78206-124 | Form: OINTMENT
Manufacturer: Organon LLC
Category: prescription | Type: HUMAN PRESCRIPTION DRUG LABEL
Date: 20251119

ACTIVE INGREDIENTS: BETAMETHASONE DIPROPIONATE 0.5 mg/1 g
INACTIVE INGREDIENTS: PROPYLENE GLYCOL; PROPYLENE GLYCOL MONOPALMITOSTEARATE; WHITE WAX; PETROLATUM

HIGHLIGHTS OF PRESCRIBING INFORMATION

These highlights do not include all the information needed to use DIPROLENE Ointment safely and effectively. See full prescribing information for DIPROLENE Ointment.
DIPROLENE® (augmented betamethasone dipropionate) ointment, for topical use
Initial U.S. Approval: 1983

1 INDICATIONS AND USAGE

DIPROLENE Ointment is a corticosteroid indicated for the relief of the inflammatory and pruritic manifestations of corticosteroid-responsive dermatoses in patients 13 years of age and older. (1)

2 DOSAGE AND ADMINISTRATION

- Apply a thin film to the affected skin areas once or twice daily. (2)
- Discontinue therapy when control is achieved. (2)
- Limit therapy to no more than 2 consecutive weeks. (2)
- Use no more than 50 g per week. (2)
- Do not use with occlusive dressings unless directed by a physician. (2)
- Avoid use on the face, groin, or axillae, or if skin atrophy is present at the treatment site. (2)
- Not for oral, ophthalmic, or intravaginal use. (2)

3 DOSAGE FORMS AND STRENGTHS

- Ointment, 0.05% (3)

4 CONTRAINDICATIONS

- Hypersensitivity to any component of this medicine. (4)

5 WARNINGS AND PRECAUTIONS

- Effects on endocrine system: DIPROLENE Ointment can cause reversible HPA axis suppression with the potential for glucocorticosteroid insufficiency during and after withdrawal of treatment. Risk factor(s) include the use of high-potency topical corticosteroids, use over a large surface area or to areas under occlusion, prolonged use, altered skin barrier, liver failure, and use in pediatric patients. Modify use should HPA axis suppression develop. (5.1, 8.4)
- Ophthalmic Adverse Reactions: DIPROLENE Ointment may increase the risk of cataracts and glaucoma. If visual symptoms occur, consider referral to an ophthalmologist for evaluation. (5.2)

6 ADVERSE REACTIONS

Most common adverse reactions (<1%) are: erythema, folliculitis, pruritus, and vesiculation. (6.1)

To report SUSPECTED ADVERSE REACTIONS, contact Organon LLC, a subsidiary of Organon & Co., at 1-844-674-3200 or FDA at 1-800-FDA-1088 or www.fda.gov/medwatch.

FULL PRESCRIBING INFORMATION

1 INDICATIONS AND USAGE

DIPROLENE® Ointment is a corticosteroid indicated for the relief of the inflammatory and pruritic manifestations of corticosteroid-responsive dermatoses in patients 13 years of age or older.

2 DOSAGE AND ADMINISTRATION

Apply a thin film of DIPROLENE Ointment to the affected skin areas once or twice daily.

Therapy should be discontinued when control is achieved. If no improvement is seen within 2 weeks, reassessment of diagnosis may be necessary. DIPROLENE Ointment is a super-high-potency topical corticosteroid. Treatment with DIPROLENE Ointment should not exceed 50 g per week because of the potential for the drug to suppress the hypothalamic-pituitary-adrenal (HPA) axis [see Warnings and Precautions (5.1)].

DIPROLENE Ointment should not be used with occlusive dressings unless directed by a physician.

Avoid use on the face, groin, or axillae, or if skin atrophy is present at the treatment site.

Avoid contact with eyes. Wash hands after each application.

DIPROLENE Ointment is for topical use only. It is not for oral, ophthalmic, or intravaginal use.

3 DOSAGE FORMS AND STRENGTHS

Ointment, 0.05%. Each gram of DIPROLENE Ointment, 0.05% contains 0.643 mg betamethasone dipropionate (equivalent to 0.5 mg betamethasone) in a white to off-white ointment base.

4 CONTRAINDICATIONS

DIPROLENE Ointment is contraindicated in patients who are hypersensitive to betamethasone dipropionate, to other corticosteroids, or to any ingredient in this preparation.

5 WARNINGS AND PRECAUTIONS

5.1 Effects on Endocrine System

DIPROLENE Ointment can produce reversible hypothalamic-pituitary-adrenal (HPA) axis suppression with the potential for glucocorticosteroid insufficiency. This may occur during treatment or after withdrawal of treatment. Factors that predispose to HPA axis suppression include the use of high-potency steroids, large treatment surface areas, prolonged use, use of occlusive dressings, altered skin barrier, liver failure, and young age. Evaluation for HPA axis suppression may be done by using the adrenocorticotropic hormone (ACTH) stimulation test.

In a trial evaluating the effects of DIPROLENE Ointment on the HPA axis, at 14 g per day, DIPROLENE Ointment was shown to suppress the plasma levels of adrenal cortical hormones following repeated application to diseased skin in subjects with psoriasis. These effects were reversible upon discontinuation of treatment. At 7 g per day, DIPROLENE Ointment was shown to cause minimal inhibition of the HPA axis when applied 2 times daily for 2 to 3 weeks in healthy subjects and in subjects with psoriasis and eczematous disorders.

With 6 g to 7 g of DIPROLENE Ointment applied once daily for 3 weeks, no significant inhibition of the HPA axis was observed in subjects with psoriasis and atopic dermatitis, as measured by plasma cortisol and 24-hour urinary 17-hydroxy-corticosteroid levels.

If HPA axis suppression is documented, gradually withdraw the drug, reduce the frequency of application, or substitute with a less potent corticosteroid. Infrequently, signs and symptoms of steroid withdrawal may occur, requiring supplemental systemic corticosteroids.

Cushing's syndrome and hyperglycemia may also occur with topical corticosteroids. These events are rare and generally occur after prolonged exposure to excessively large doses, especially of high-potency topical corticosteroids.

Pediatric patients may be more susceptible to systemic toxicity due to their larger skin surface to body mass ratios [see Use in Specific Populations (8.4)].

5.2 Ophthalmic Adverse Reactions

Use of topical corticosteroids, including DIPROLENE Ointment, may increase the risk of posterior subcapsular cataracts and glaucoma. Cataracts and glaucoma have been reported postmarketing with the use of topical corticosteroid products, including DIPROLENE Ointment [see Adverse Reactions (6.2)].

Avoid contact of DIPROLENE Ointment with eyes. Advise patients to report any visual symptoms and consider referral to an ophthalmologist for evaluation.

5.3 Allergic Contact Dermatitis

Allergic contact dermatitis with corticosteroids is usually diagnosed by observing failure to heal rather than noting a clinical exacerbation. Such an observation should be corroborated with appropriate diagnostic patch testing. If irritation develops, topical corticosteroids should be discontinued and appropriate therapy instituted.

6 ADVERSE REACTIONS

6.1 Clinical Trials Experience

Because clinical trials are conducted under widely varying conditions, adverse reaction rates observed in the clinical trials of a drug cannot be directly compared to rates in the clinical trials of another drug and may not reflect the rates observed in clinical practice.

In controlled clinical trials, adverse reactions associated with the use of DIPROLENE Ointment reported at a frequency of less than 1% included erythema, folliculitis, pruritus, and vesiculation.

6.2 Postmarketing Experience

Because adverse reactions are reported voluntarily from a population of uncertain size, it is not always possible to reliably estimate their frequency or establish a causal relationship to drug exposure.

Postmarketing reports for local adverse reactions to topical corticosteroids may also include: skin atrophy, telangiectasias, burning, irritation, dryness, acneiform eruptions, hypopigmentation, perioral dermatitis, allergic contact dermatitis, secondary infection, hypertrichosis, striae, and miliaria.

Hypersensitivity reactions, consisting of predominantly skin signs and symptoms, e.g., contact dermatitis, pruritus, bullous dermatitis, and erythematous rash have been reported.

Ophthalmic adverse reactions of cataracts, glaucoma, increased intraocular pressure, and central serous chorioretinopathy have been reported with the use of topical corticosteroids, including topical betamethasone products.

8 USE IN SPECIFIC POPULATIONS

8.1 Pregnancy

Risk Summary

There are no available data on DIPROLENE Ointment use in pregnant women to identify a drug-associated risk of major birth defects, miscarriage, or adverse maternal or fetal outcomes.

Observational studies suggest an increased risk of low birthweight infants with the use of greater than 300 grams of potent or very potent topical corticosteroid during a pregnancy. Advise pregnant women that DIPROLENE Ointment may increase the risk of having a low birthweight infant and to use DIPROLENE Ointment on the smallest area of skin and for the shortest duration possible.

In animal reproduction studies, increased malformations, including umbilical hernias, cephalocele, and cleft palate, were observed after intramuscular administration of betamethasone dipropionate to pregnant rabbits. The available data do not allow the calculation of relevant comparisons between the systemic exposure of betamethasone dipropionate in animal studies to the systemic exposure that would be expected in humans after topical use of DIPROLENE Ointment (see Data).

The background risk of major birth defects and miscarriage for the indicated population is unknown. All pregnancies have a background risk of birth defect, loss, or other adverse outcomes. In the U.S. general population, the estimated risk of major birth defects and miscarriage in clinically recognized pregnancies is 2 to 4% and 15 to 20%, respectively.

Data

Animal Data

Betamethasone dipropionate has been shown to cause malformations in rabbits when given by the intramuscular route at doses of 0.05 mg/kg. The abnormalities observed included umbilical hernias, cephalocele, and cleft palate.

8.2 Lactation

Risk Summary

There are no data regarding the presence of betamethasone dipropionate in human milk, the effects on the breastfed infant, or the effects on milk production after topical application of DIPROLENE Ointment to women who are breastfeeding.

It is possible that topical administration of betamethasone dipropionate could result in sufficient systemic absorption to produce detectable quantities in human milk. The developmental and health benefits of breastfeeding should be considered along with the mother's clinical need for DIPROLENE Ointment and any potential adverse effects on the breastfed infant from DIPROLENE Ointment or from the underlying maternal condition.

Clinical Considerations

To minimize potential exposure to the breastfed infant via breast milk, use DIPROLENE Ointment on the smallest area of skin and for the shortest duration possible while breastfeeding. Advise breastfeeding women not to apply DIPROLENE Ointment directly to the nipple and areola to avoid direct infant exposure [see Use in Specific Populations (8.4)].

8.4 Pediatric Use

Use of DIPROLENE Ointment in pediatric patients younger than 13 years of age is not recommended due to the potential for HPA axis suppression [see Warnings and Precautions (5.1)].

In an open-label HPA axis safety trial in subjects 3 months to 12 years of age with atopic dermatitis, DIPROLENE AF Cream 0.05% was applied twice daily for 2 to 3 weeks over a mean body surface area of 58% (range 35% to 95%). In 19 of 60 (32%) evaluable subjects, adrenal suppression was indicated by either a ≤5 mcg/dL pre-stimulation cortisol, or a cosyntropin post-stimulation cortisol ≤18 mcg/dL and/or an increase of <7 mcg/dL from the baseline cortisol. Out of the 19 subjects with HPA axis suppression, 4 subjects were tested 2 weeks after discontinuation of DIPROLENE AF Cream, and 3 of the 4 (75%) had complete recovery of HPA axis function. The proportion of subjects with adrenal suppression in this trial was progressively greater, the younger the age group.

Because of a higher ratio of skin surface area to body mass, pediatric patients are at a greater risk than adults of systemic toxicity when treated with topical drugs. They are, therefore, also at greater risk of HPA axis suppression and adrenal insufficiency upon the use of topical corticosteroids.

Rare systemic effects such as Cushing's syndrome, linear growth retardation, delayed weight gain, and intracranial hypertension have been reported in pediatric patients, especially those with prolonged exposure to large doses of high potency topical corticosteroids.

Local adverse reactions including skin atrophy have also been reported with use of topical corticosteroids in pediatric patients.

Avoid use of DIPROLENE Ointment in the treatment of diaper dermatitis.

8.5 Geriatric Use

Clinical trials of DIPROLENE Ointment included 225 subjects who were 65 years of age and over and 46 subjects who were 75 years of age and over. No overall differences in safety or effectiveness were observed between these subjects and younger subjects, and other reported clinical experience has not identified differences in responses between the elderly and younger patients. However, greater sensitivity of some older individuals cannot be ruled out.

11 DESCRIPTION

DIPROLENE (augmented betamethasone dipropionate) Ointment, 0.05% contains betamethasone dipropionate USP, a synthetic adrenocorticosteroid, for topical use. Betamethasone, an analog of prednisolone, has a high degree of corticosteroid activity and a slight degree of mineralocorticoid activity. Betamethasone dipropionate is the 17, 21-dipropionate ester of betamethasone.

Chemically, betamethasone dipropionate is 9-fluoro-11β, 17,21-trihydroxy-16β -methylpregna-1,4-diene-3,20-dione 17,21-dipropionate, with the empirical formula C28H37FO7, a molecular weight of 504.6 and the following structural formula:

It is a white to creamy-white, odorless powder insoluble in water; freely soluble in acetone and in chloroform; sparingly soluble in alcohol.

Each gram of DIPROLENE Ointment, 0.05% contains 0.643 mg betamethasone dipropionate USP (equivalent to 0.5 mg betamethasone), in a white ointment base of propylene glycol; propylene glycol stearate; white petrolatum; and white wax.

12 CLINICAL PHARMACOLOGY

12.1 Mechanism of Action

Corticosteroids play a role in cellular signaling, immune function, inflammation, and protein regulation; however, the precise mechanism of action of DIPROLENE Ointment in corticosteroid responsive dermatoses is unknown.

12.2 Pharmacodynamics

Vasoconstrictor Assay

Trials performed with DIPROLENE Ointment, 0.05% indicate that it is in the super-high range of potency as demonstrated in vasoconstrictor trials in healthy subjects when compared with other topical corticosteroids. However, similar blanching scores do not necessarily imply therapeutic equivalence.

12.3 Pharmacokinetics

No pharmacokinetics trials have been conducted with DIPROLENE Ointment.

The extent of percutaneous absorption of topical corticosteroids is determined by many factors including the vehicle, the integrity of the epidermal barrier, and the use of occlusive dressings.

Topical corticosteroids can be absorbed through normal intact skin. Inflammation and/or other disease processes in the skin may increase percutaneous absorption. Occlusive dressings substantially increase the percutaneous absorption of topical corticosteroids [see Dosage and Administration (2)].

Once absorbed through the skin, topical corticosteroids enter pharmacokinetic pathways similar to systemically administered corticosteroids. Corticosteroids are bound to plasma proteins in varying degrees, are metabolized primarily in the liver, and excreted by the kidneys. Some of the topical corticosteroids and their metabolites are also excreted into the bile.

13 NONCLINICAL TOXICOLOGY

13.1 Carcinogenesis, Mutagenesis, Impairment of Fertility

Long-term animal studies have not been performed to evaluate the carcinogenic potential of betamethasone dipropionate.

Betamethasone was negative in the bacterial mutagenicity assay (Salmonella typhimurium and Escherichia coli), and in the mammalian cell mutagenicity assay (CHO/HGPRT). It was positive in the in vitro human lymphocyte chromosome aberration assay, and equivocal in the in vivo mouse bone marrow micronucleus assay.

Studies in rabbits, mice, and rats using intramuscular doses up to 1, 33, and 2 mg/kg, respectively, resulted in dose-related increases in fetal resorptions in rabbits and mice.

14 CLINICAL STUDIES

The safety and efficacy of DIPROLENE Ointment for the treatment of corticosteroid-responsive dermatoses, psoriasis and atopic dermatitis, have been evaluated in three randomized active-controlled trials, two in psoriasis and one in atopic dermatitis. A total of 378 subjects, of whom 152 received DIPROLENE Ointment, were included in these trials. These trials evaluated DIPROLENE Ointment applied twice daily, for 14 days. DIPROLENE Ointment was shown to be effective in relieving signs and symptoms of psoriasis and atopic dermatitis.

16 HOW SUPPLIED/STORAGE AND HANDLING

DIPROLENE Ointment 0.05% is a white ointment supplied in 15-g (NDC 78206-124-01) and 50-g (NDC 78206-124-02) tubes.

STORAGE AND HANDLING

Store at 25°C (77°F); excursions permitted to 15-30°C (59-86°F) [see USP Controlled Room Temperature].

17 PATIENT COUNSELING INFORMATION

Advise the patient to read the FDA-approved patient labeling (Patient Information).

Inform patients of the following:

- Discontinue therapy when control is achieved, unless directed otherwise by the physician.
- Use no more than 50 grams per week of DIPROLENE Ointment and no longer than 2 consecutive weeks.
- Avoid contact with the eyes.
- Advise patients to report any visual symptoms to their healthcare providers.
- Avoid use of DIPROLENE Ointment on the face, underarms, or groin areas unless directed by the physician.
- Do not occlude the treatment area with bandage or other covering, unless directed by the physician.
- Note that local reactions and skin atrophy are more likely to occur with occlusive use, prolonged use or use of higher potency corticosteroids.
- Advise a woman to use DIPROLENE Ointment on the smallest area of skin and for the shortest duration possible while pregnant or breastfeeding. Advise breastfeeding women not to apply DIPROLENE Ointment directly to the nipple and areola to avoid direct infant exposure.

Distributed by: Organon LLC, a subsidiary of
ORGANON & Co.,
Jersey City, NJ 07302, USA

For patent information: www.organon.com/our-solutions/patent/

© 2022 Organon group of companies. All rights reserved.

uspi-og1460-ot-2202r001

Patient Information
DIPROLENE® (DIH-pro-leen)
(augmented betamethasone dipropionate) Ointment

Important information: DIPROLENE Ointment is for use on skin only. Do not use DIPROLENE Ointment in your eyes, mouth, or vagina.

What is DIPROLENE Ointment?
DIPROLENE Ointment is a prescription corticosteroid medicine used on the skin (topical) for the relief of redness, swelling, heat, pain (inflammation) and itching, caused by certain skin problems in people 13 years of age and older.

- DIPROLENE Ointment should not be used in children under 13 years of age.

Do not use DIPROLENE Ointment if you are allergic to betamethasone dipropionate or any of the ingredients in DIPROLENE Ointment. See the end of this leaflet for a complete list of ingredients in DIPROLENE Ointment.

Before using DIPROLENE Ointment, tell your healthcare provider about all of your medical conditions, including if you:

- have had irritation or other skin reaction to a steroid medicine in the past.
- have thinning of the skin (atrophy) at the treatment site.
- have diabetes.
- have adrenal gland problems.
- have liver problems.
- have cataracts or glaucoma.
- are pregnant or plan to become pregnant. It is not known if DIPROLENE Ointment will harm your unborn baby. If you use DIPROLENE Ointment during pregnancy, use DIPROLENE Ointment on the smallest area of the skin and for the shortest time needed.
- are breastfeeding or plan to breastfeed. It is not known if DIPROLENE Ointment passes into your breast milk. Breastfeeding women should use DIPROLENE Ointment on the smallest area of skin and for the shortest time needed while breastfeeding. Do not apply DIPROLENE Ointment directly to the nipple and areola to avoid contact with your baby.

Tell your healthcare provider about all the medicines you take, including prescription and over-the-counter medicines, vitamins, and herbal supplements.

Especially tell your healthcare provider if you take other corticosteroid medicines by mouth or injection or use other products on your skin or scalp that contain corticosteroids.

Do not use other products containing a steroid medicine with DIPROLENE Ointment without talking to your healthcare provider first.

How should I use DIPROLENE Ointment?

- Use DIPROLENE Ointment exactly as your healthcare provider tells you to use it.
- Apply a thin layer (film) of DIPROLENE Ointment to the affected skin area 1 or 2 times each day. Do not use more than 50 grams of DIPROLENE Ointment in 1 week.
- Do not use DIPROLENE Ointment for longer than 2 weeks in a row unless your healthcare provider tells you to.
- Tell your healthcare provider if the treated skin area does not get better after 2 weeks of treatment with DIPROLENE Ointment.
- Do not bandage, cover, or wrap the treated skin area unless your healthcare provider tells you to.
- DIPROLENE Ointment should not be used to treat diaper rash or redness.
- Avoid using DIPROLENE Ointment on the face, groin, or underarms (armpits) or if thinning of the skin (atrophy) is present at the treatment site.
- Wash your hands after applying DIPROLENE Ointment unless you are using the medicine to treat your hands.

What are the possible side effects of DIPROLENE Ointment?
DIPROLENE Ointment may cause serious side effects, including:

- DIPROLENE Ointment can pass through your skin. Too much DIPROLENE Ointment passing through your skin can cause your adrenal glands to stop working properly. Your healthcare provider may do blood tests to check for adrenal gland problems.
- Cushing's syndrome, a condition that happens when your body is exposed to too much of the hormone cortisol.
- High blood sugar (hyperglycemia).
- Effects on growth and weight in children.
- Vision problems. Topical corticosteroids including DIPROLENE Ointment may increase your chance of developing cataract(s) and glaucoma. Tell your healthcare provider if you develop blurred vision or other vision problems during treatment with DIPROLENE Ointment.
- Skin problems. Skin problems including, allergic reactions (contact dermatitis) may happen during treatment with DIPROLENE Ointment. Stop using DIPROLENE Ointment and tell your healthcare provider if you develop any skin reactions or have problems with healing during treatment with DIPROLENE Ointment.

Your healthcare provider may do certain blood tests to check for side effects.

The most common side effects of DIPROLENE Ointment include redness of the skin, inflamed hair follicles, itching and blistering.

These are not all of the possible side effects of DIPROLENE Ointment.

Call your doctor for medical advice about side effects. You may report side effects to FDA at 1-800-FDA-1088.

How should I store DIPROLENE Ointment?

- Store DIPROLENE Ointment at room temperature between 68°F to 77°F (20°C to 25°C).
- Keep DIPROLENE Ointment and all medicines out of the reach of children.

General information about the safe and effective use of DIPROLENE Ointment.
Medicines are sometimes prescribed for purposes other than those listed in a Patient Information leaflet. Do not use DIPROLENE Ointment for a condition for which it was not prescribed. Do not give DIPROLENE Ointment to other people, even if they have the same symptoms that you have. It may harm them. You can ask your pharmacist or healthcare provider for information about DIPROLENE Ointment that is written for health professionals.

What are the ingredients in DIPROLENE Ointment?

Active ingredient: augmented betamethasone dipropionate
Inactive ingredients: propylene glycol; propylene glycol stearate; white petrolatum; and white wax.

Distributed by: Organon LLC, a subsidiary of
ORGANON & Co.,
Jersey City, NJ 07302, USA

© 2022 Organon group of companies. All rights reserved.
usppi-og1460-ot-2202r001
For patent information: www.organon.com/our-solutions/patent/

This Patient Information has been approved by the U.S. Food and Drug Administration.

Revised: 2/2022

PRINCIPAL DISPLAY PANEL - 15 g Tube Box

NDC 78206-124-01

15 g

Diprolene®

(augmented
betamethasone
dipropionate)

Ointment, 0.05%*

*Strength expressed
as betamethasone

For topical
use only.

Not for oral,
ophthalmic, or
intravaginal use.

Rx only